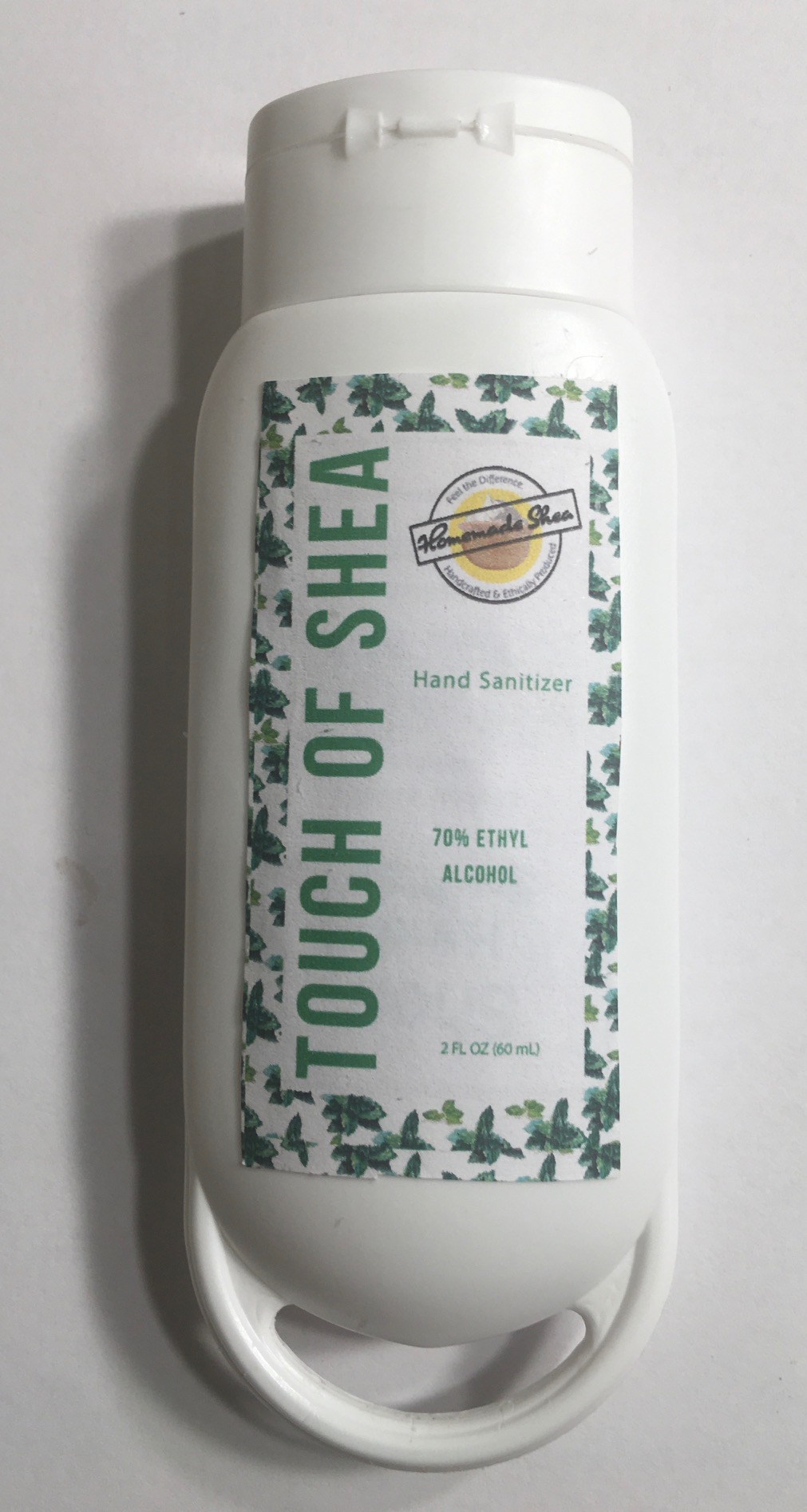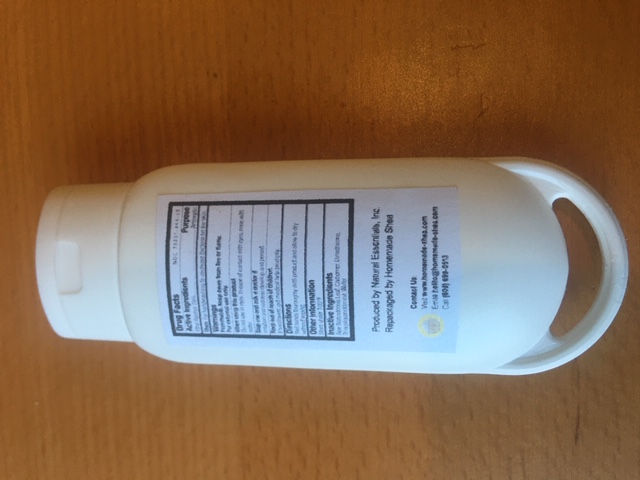 DRUG LABEL: Touch of Shea Hand Sanitizer
NDC: 78401-444 | Form: GEL
Manufacturer: Homemade Shea LLC
Category: otc | Type: HUMAN OTC DRUG LABEL
Date: 20200604

ACTIVE INGREDIENTS: ALCOHOL 0.7 mL/1 mL
INACTIVE INGREDIENTS: GLYCERIN; POLYACRYLIC ACID (8000 MW); WATER; ALOE VERA LEAF; ISOPROPYL ALCOHOL; PROPYLENE GLYCOL; .ALPHA.-TOCOPHEROL ACETATE

Flammable. Keep away from fire or flame. For external use only.

Warning: Flammable. Keep away from fire or flame. For external use only.

Ethyl Alcohol 70% Purpose: Antiseptic

Do not use in eyes. In case of contact with eyes, rinse with water.

When using this product

Do not use in eyes. In case of contact with eyes, rinse with water.

irritation and redness develop and persist.

ask doctor if irritation and redness develop and persist

If swallowed, get medical help promptly.

Inactive Ingredients

WATER

ISOPROPYL ALCOHOL

GLYCERIN

POLYACRYLIC ACID

PROPYLENE GLYCOL

.ALPHA.-TOCOPHEROL ACETATE

ALOE VERA LEAF

Other Information - Store under 105°F

Store Under 105ºF

Uses

For handwashing to decrease bacteria on the skin

Wet hands thoroughly with product and allow to dry without wiping.

Purpose

Antiseptic